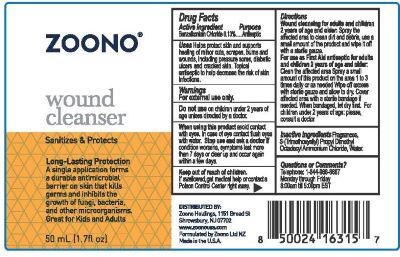 DRUG LABEL: Zoono Wound Cleanser
NDC: 69221-204 | Form: SOLUTION
Manufacturer: Zoono Holdings USA LLC
Category: otc | Type: HUMAN OTC DRUG LABEL
Date: 20250828

ACTIVE INGREDIENTS: BENZALKONIUM CHLORIDE 0.13 g/100 mL
INACTIVE INGREDIENTS: WATER

Zoono Wound Cleanser

Active Ingredient

Benzalkonium Chloride 0.13%

Purpose:

Antiseptic

Uses:

Helps protect skin and supports healing

of minor cuts, scrapes, burns and wounds,

including pressure sores, diabetic ulcers,

cracked skin and lips. Topical antiseptic to help

decrease the risk of skin infections.

Warnings:

For external use only.

Do not use on children under 2 years of age unless directed by a doctor.

When using this product avoid contact with

eyes. In case of eye contact flush eyes with

water. Stop use and ask a doctor if condition

worsens, symptoms last more than 7 days or

clear up and occur again within a few days.

Keep out of reach of children. If swallowed, get medical help or contact a

Poison Control Center right away.

Inactive Ingredients:

Fragrances, Silica Complex 3-(Trimethoxysilyl) Propyl Dimethyl Octadecyl Ammonium Chloride), Water.

Questions or Comments?

Telephone 1-844-966-6687

Monday through Friday

8:00am till 5:00pm EST

Directions:

Wound cleansing for adults and children 2

years of age or older: Spray the affected area

to clean dirt and debris, use a small amount of

the product and wipe it off with a sterile gauze.

For use as First Aid antiseptic for adults and

children years of age or older:

Clean the affected area. Spray a small amount of

this product on the area 1 to 3 times daily or as

needed. Wipe off excess with sterile gauze and

allow to dry. Cover affected area with a sterile

bandage if needed. When bandaged, let dry first

For children under 2 years of age please

consult a doctor.